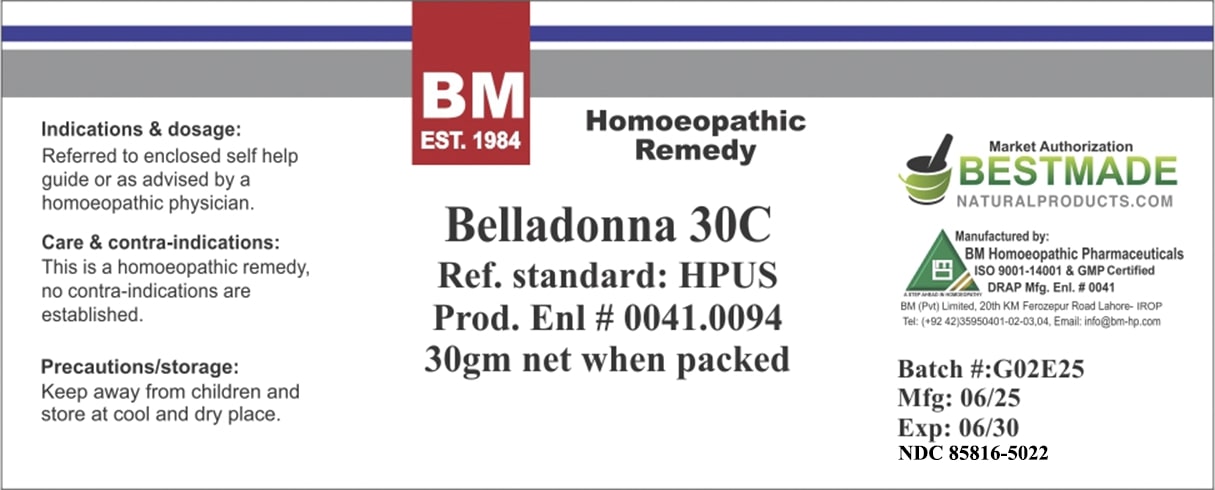 DRUG LABEL: BM Belladonna
NDC: 85816-5022 | Form: GLOBULE
Manufacturer: BM Private Limited
Category: homeopathic | Type: HUMAN OTC DRUG LABEL
Date: 20250701

ACTIVE INGREDIENTS: ATROPA BELLADONNA 30 [hp_C]/1 g
INACTIVE INGREDIENTS: SUCROSE 1 g/1 g

BM Belladonna 30C

INACTIVE INGREDIENT

Sucrose

ACTIVE INGREDIENT

Belladonna

Indications & dosage: As advised by a homoeopathic physician.

Indications & dosage: As advised by a homoeopathic physician.

PURPOSE

Indications & dosage: As advised by a homoeopathic physician.

CONTRAINDICATIONS

Care & contra-indications: This is a homoeopathic product, no contra-indications are established.

WARNINGS

Precautions/storage: Keep away from children and store at cool and dry place.

KEEP OUT OF REACH OF CHILDREN

Precautions/storage: Keep away from children and store at cool and dry place.

STORAGE AND HANDLING

Precautions/storage: Keep away from children and store at cool and dry place.

Entire package label